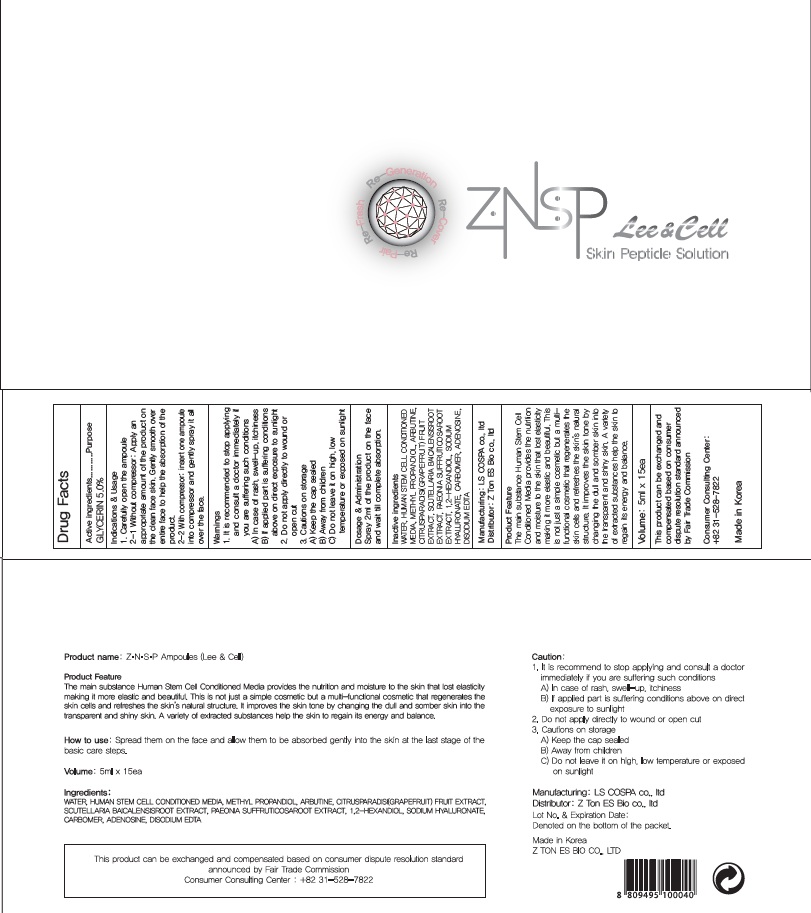 DRUG LABEL: ZNSP Ampoule
NDC: 70749-010 | Form: SOLUTION
Manufacturer: Z-TON ES BIO CO., LTD.
Category: otc | Type: HUMAN OTC DRUG LABEL
Date: 20160602

ACTIVE INGREDIENTS: GLYCERIN 0.25 g/5 mL
INACTIVE INGREDIENTS: WATER; METHYLPROPANEDIOL

ACTIVE INGREDIENT

Active Ingredient: GLYCERIN 5.0%

INACTIVE INGREDIENT

Inactive Ingredients: WATER, ACETYL HEXAPEPTIDE-8, Methyl PROPANDIOL, ARBUTINE, CITRUSPARADISI(GRAPEFRUIT)FRUIT EXTRACT, SCUTELLARIA BAICALENSISROOT EXTRACT, PAEONIA SUFFRUTICOSAROOT EXTRACT, 1,2-HEXANDIOL, SODIUM HYALURONATE, CARBOMER, ADENOSINE, DISODIUM EDTA

PURPOSE

Purpose: Skin Protectant

WARNINGS

Warnings: 1. It is recommended to stop applying and consult a doctor immediately if you are suffering such conditions A) In case of rash, swell-up, itchiness B) If applied part is suffering conditions above on direct exposure to sunlight 2. Do not apply directly to wound or open cut 3. Cautions on storage A) Keep the cap sealed B) Away from children C) Do not leave it on high, low temperature or exposed on sunlight

KEEP OUT OF REACH OF CHILDREN

INDICATIONS & USAGE

Indications & usage: 1. Carefully open the ampoule

2-1. Without compressor: Apply an appropriate amount of the product on the clean face skin. Gently smooth over entire face to help the absorption of the product.

2-2. With compressor: insert one ampoule into compressor and gently spray it all over the face.

DOSAGE & ADMINISTRATION

Dosage & Administration: Apply 2ml per each time; gently wrap your skin to help absorption